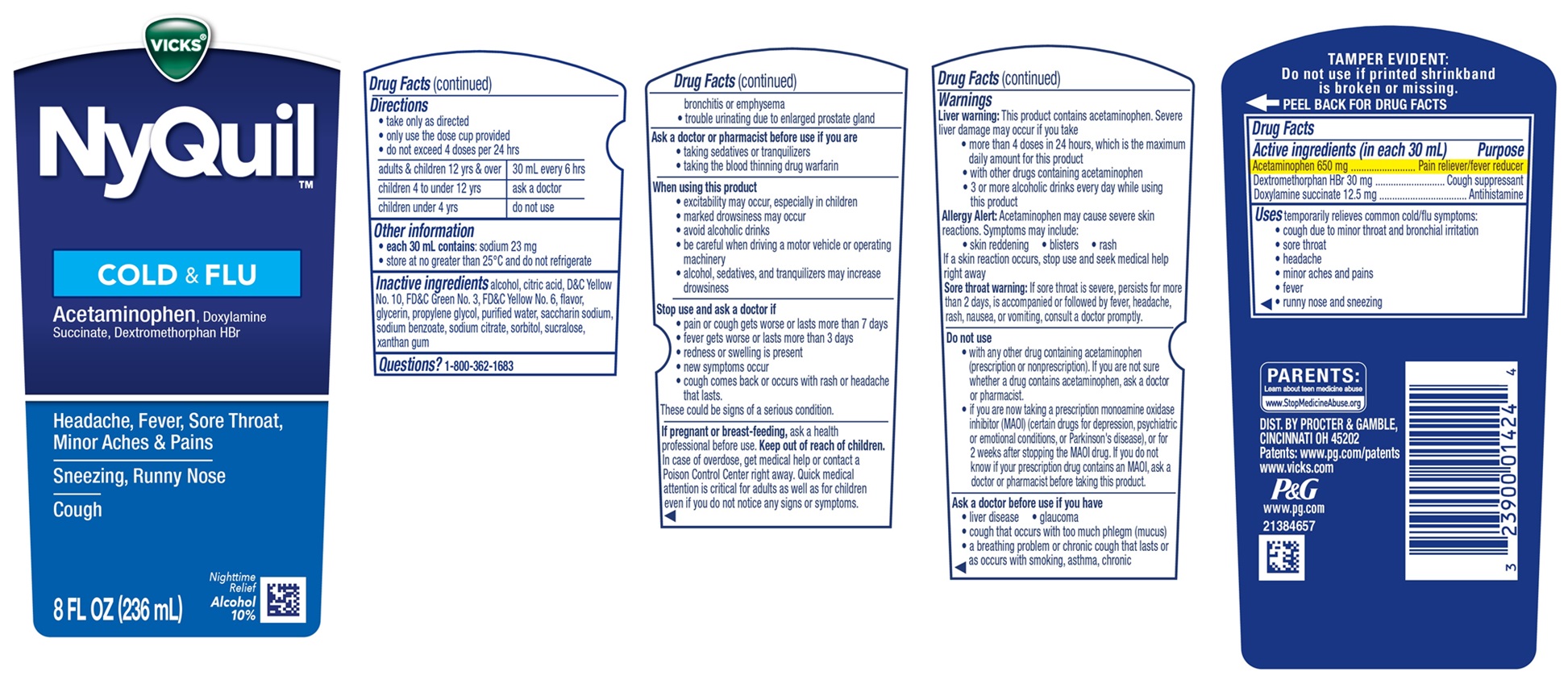 DRUG LABEL: Vicks NyQuil
NDC: 69423-789 | Form: LIQUID
Manufacturer: The Procter & Gamble Manufacturing Company
Category: otc | Type: HUMAN OTC DRUG LABEL
Date: 20251203

ACTIVE INGREDIENTS: ACETAMINOPHEN 650 mg/30 mL; DEXTROMETHORPHAN HYDROBROMIDE 30 mg/30 mL; DOXYLAMINE SUCCINATE 12.5 mg/30 mL
INACTIVE INGREDIENTS: ALCOHOL; CITRIC ACID MONOHYDRATE; D&C YELLOW NO. 10; FD&C GREEN NO. 3; FD&C YELLOW NO. 6; PROPYLENE GLYCOL; WATER; SACCHARIN SODIUM; SODIUM BENZOATE; SODIUM CITRATE; XANTHAN GUM; GLYCERIN; SUCRALOSE; SORBITOL

VICKS® NyQuil ™ COLD & FLU

Drug Facts

Active ingredients (in each 30 mL dose cup)

Acetaminophen 650 mg

Dextromethorphan HBr 30 mg

Doxylamine succinate 12.5 mg

Purpose

Pain reliever/fever reducer

Cough suppressant

Antihistamine

Uses

temporarily relieves common cold/flu symptoms:

- cough due to minor throat and bronchial irritation
- sore throat
- headache
- minor aches and pains
- fever
- runny nose and sneezing

Warnings

Liver warning:

This product contains acetaminophen. Severe liver damage may occur if you take

- more than 4 doses in 24 hours, which is the maximum daily amount for this product
- with other drugs containing acetaminophen
- 3 or more alcoholic drinks every day while using this product

Allergy Alert:

Acetaminophen may cause severe skin reactions.

Symptoms may include:

- skin reddening
- blisters
- rash

If a skin reaction occurs, stop use and seek medical help right away

Sore throat warning:

If sore throat is severe, lasts for more than 2 days, occurs with or is followed by fever, headache, rash, nausea, or vomiting, see a doctor promptly.

Do not use

- with any other drug containing acetaminophen (prescription or nonprescription). If you are not sure whether a drug contains acetaminophen, ask a doctor or pharmacist.
- if you are now taking a prescription monoamine oxidase inhibitor (MAOI) (certain drugs for depression, psychiatric or emotional conditions, or Parkinson's disease), or for 2 weeks after stopping the MAOI drug. If you do not know if your prescription drug contains an MAOI, ask a doctor or pharmacist before taking this product.

Ask a doctor before use if you have

- liver disease
- glaucoma
- cough that occurs with too much phlegm (mucus)
- a breathing problem or chronic cough that lasts or as occurs with smoking, asthma, chronic bronchitis or emphysema
- trouble urinating due to enlarged prostate gland

Ask a doctor or pharmacist before use if you are

- taking sedatives or tranquilizers
- taking the blood thinning drug warfarin

When using this product

- excitability may occur, especially in children
- marked drowsiness may occur
- avoid alcoholic drinks
- be careful when driving a motor vehicle or operating machinery
- alcohol, sedatives, and tranquilizers may increase drowsiness

Stop use and ask a doctor if

- pain or cough gets worse or lasts more than 7 days
- fever gets worse or lasts more than 3 days
- redness or swelling is present
- new symptoms occur
- cough comes back or occurs with rash or headache that lasts.

These could be signs of a serious condition.

PREGNANCY OR BREAST FEEDING

If pregnant or breast-feeding, ask a health professional before use.

Keep out of reach of children.

In case of overdose, get medical help or contact a Poison Control Center right away. Quick medical attention is critical for adults as well as for children even if you do not notice any signs or symptoms.

Directions

• take only as directed
• only use the dose cup provided
• do not exceed 4 doses per 24 hrs

adults & children 12 yrs & over | 30 mL every 6 hrs
children 4 to under 12 yrs | ask a doctor
children under 4 yrs | do not use

Other information

- each 30 mL dose cup contains:sodium 23 mg
- store at no greater than 25°C and do not refrigerate

Inactive ingredients

alcohol, citric acid, D&C Yellow No. 10, FD&C Green No. 3, FD&C Yellow No. 6, flavor, glycerin, propylene glycol, purified water, saccharin sodium,

sodium benzoate, sodium citrate, sorbitol, sucralose, xanthan gum

Questions?

1-800-362-1683

TAMPER EVIDENT: Do not use if printed shrinkband is broken or missing.

DIST. BY

PROCTER & GAMBLE,

CINCINNATI, OH 45202

PRINCIPAL DISPLAY PANEL - 236 ml Bottle Label

VICKS ®

NyQuil ™

COLD & FLU

Nighttime Relief

Acetaminophen, Doxylamine Succinate, Dextromethorphan HBr

Headache, Fever, Sore Throat, Minor Aches & Pains
Sneezing, Runny Nose
Cough

Nighttime Relief

Alcohol 10%

8 FL OZ (236 ml)